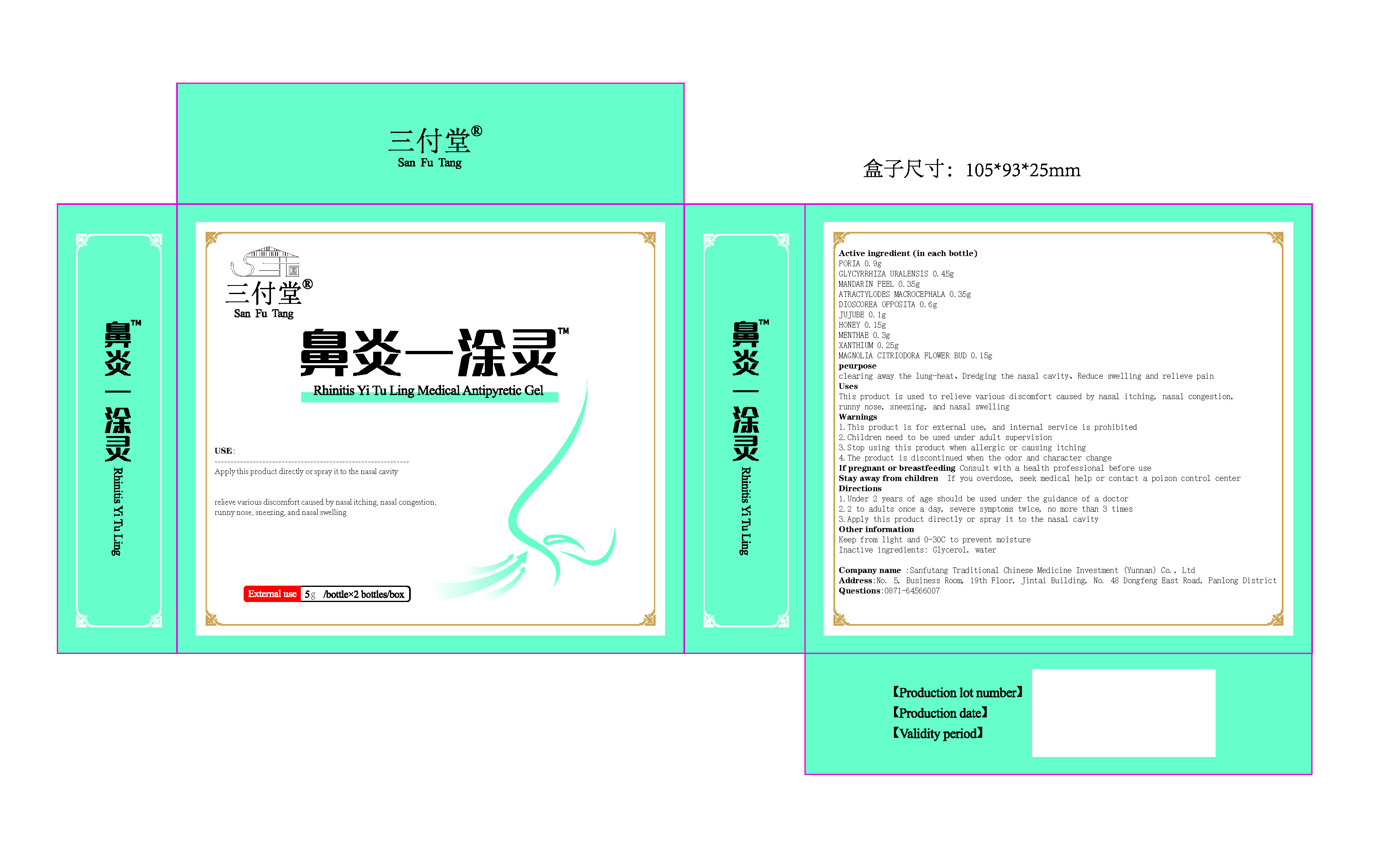 DRUG LABEL: Rhinitis Yituling
NDC: 83582-001 | Form: GEL
Manufacturer: Sanfutang Traditional Chinese Medicine Investment (Yunnan) Co., Ltd
Category: otc | Type: HUMAN OTC DRUG LABEL
Date: 20230727

ACTIVE INGREDIENTS: TANGERINE PEEL 7 g/100 g; XANTHIUM SIBIRICUM FRUIT 5 g/100 g; ATRACTYLODES MACROCEPHALA WHOLE 7 g/100 g; CHINESE YAM 12 g/100 g; JUJUBE FRUIT 2 g/100 g; HONEY 3 g/100 g; MENTHA ARVENSIS LEAF 6 g/100 g; FU LING 18 g/100 g; GLYCYRRHIZA URALENSIS 9 g/100 g; MAGNOLIA DENUDATA FLOWER BUD 3 g/100 g
INACTIVE INGREDIENTS: GLYCERIN; WATER

Active ingredient

PORIA, GLYCYRRHIZA URALENSIS, MANDARIN PEEL, ATRACTYLODES MACROCEPHALA, DIOSCOREA OPPOSITA, JUJUBE

, HONEY, MENTHAE, XANTHIUM, MAGNOLIA CITRIODORA FLOWER BUD

peurpose

clearing away the lung-heat、Dredging the nasal cavity、Reduce swelling and relieve pain

Uses

This product is used to relieve various discomfort caused by nasal itching, nasal congestion, runny nose, sneezing, and nasal swelling

Warnings

1.This product is for external use, and internal service is prohibited

2.Children need to be used under adult supervision

3.Stop using this product when allergic or causing itching

4.The product is discontinued when the odor and character change

If pregnant or breastfeeding

Consult with a health professional before use

Stay away from children

If you overdose, seek medical help or contact a poison control center

Directions

1.Under 2 years of age should be used under the guidance of a doctor

2.2 to adults once a day, severe symptoms twice, no more than 3 times

3.Apply this product directly or spray it to the nasal cavity

Inactive ingredients

Glycerol, water